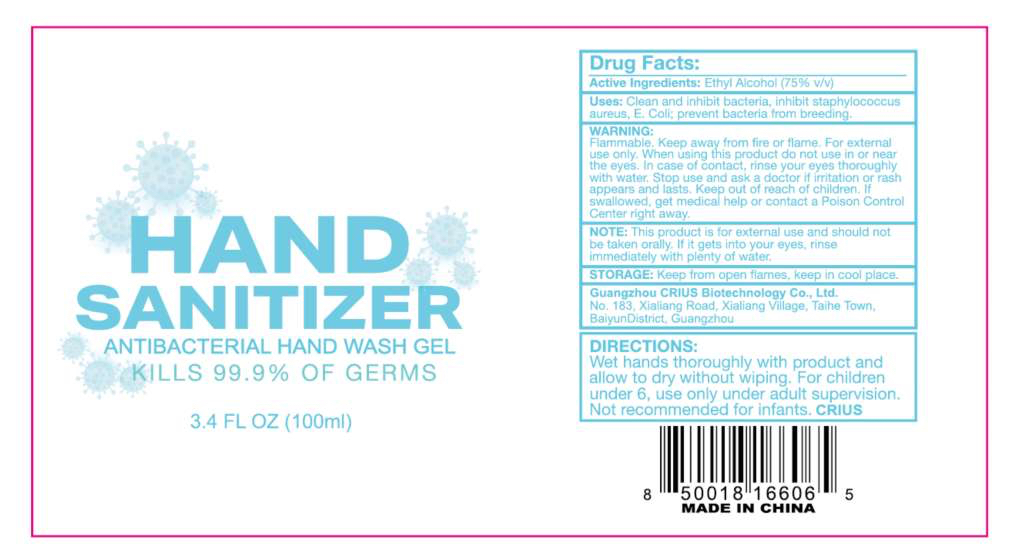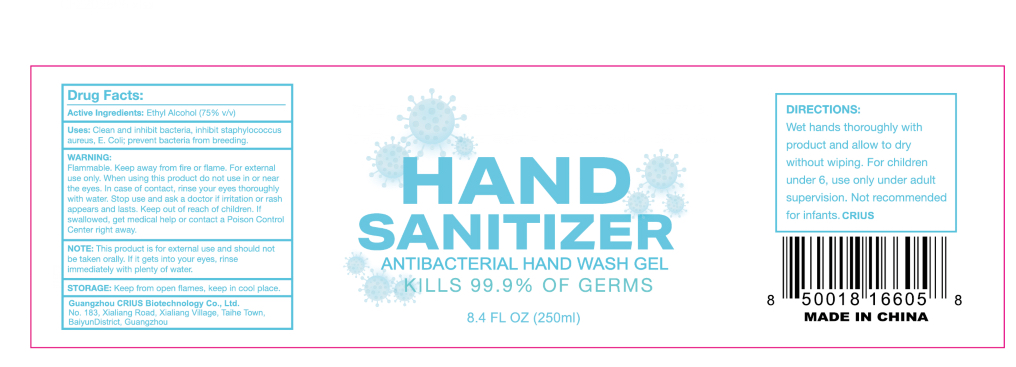 DRUG LABEL: Disposable Antibacterial Hand Wash Gel
NDC: 54158-002 | Form: GEL
Manufacturer: Guangzhou CRIUS Biotechnology Co., Ltd.
Category: otc | Type: HUMAN OTC DRUG LABEL
Date: 20200629

ACTIVE INGREDIENTS: ALCOHOL 75 mL/100 mL
INACTIVE INGREDIENTS: AMINOMETHYLPROPANOL; GLYCERIN; CARBOMER HOMOPOLYMER, UNSPECIFIED TYPE; WATER

Active Ingredient(s)

Ethanol Alcohol 75% v/v. Purpose: Antiseptic

Purpose

Antiseptic, Hand Sanitizer

Warnings

For external use only. Flammable. Keep away from heat or flame

Do not use

- in children less than 2 months of age
- on open skin wounds

WHEN USING

When using this product keep out of eyes, ears, and mouth. In case of contact with eyes, rinse eyes thoroughly with water.
Stop use and ask a doctor if irritation or rash occurs. These may be signs of a serious condition.
Keep out of reach of children. If swallowed, get medical help or contact a Poison Control Center right away.

Stop use and ask a doctor if irritation or rash occurs. These may be signs of a serious condition.

Keep out of reach of children. If swallowed, get medical help or contact a Poison Control Center right away.

Directions

- Place enough product on hands to cover all surfaces. Rub hands together until dry.
- Supervise children under 6 years of age when using this product to avoid swallowing.

Other information

- keep in a cool place.

Inactive ingredients

Water,Glycerol,Carbomer,AMINOMETHYL PROPANOL

Package Label - Principal Display Panel

100ML NDC: 54158-002-10

250ML NDC: 54158-002-25